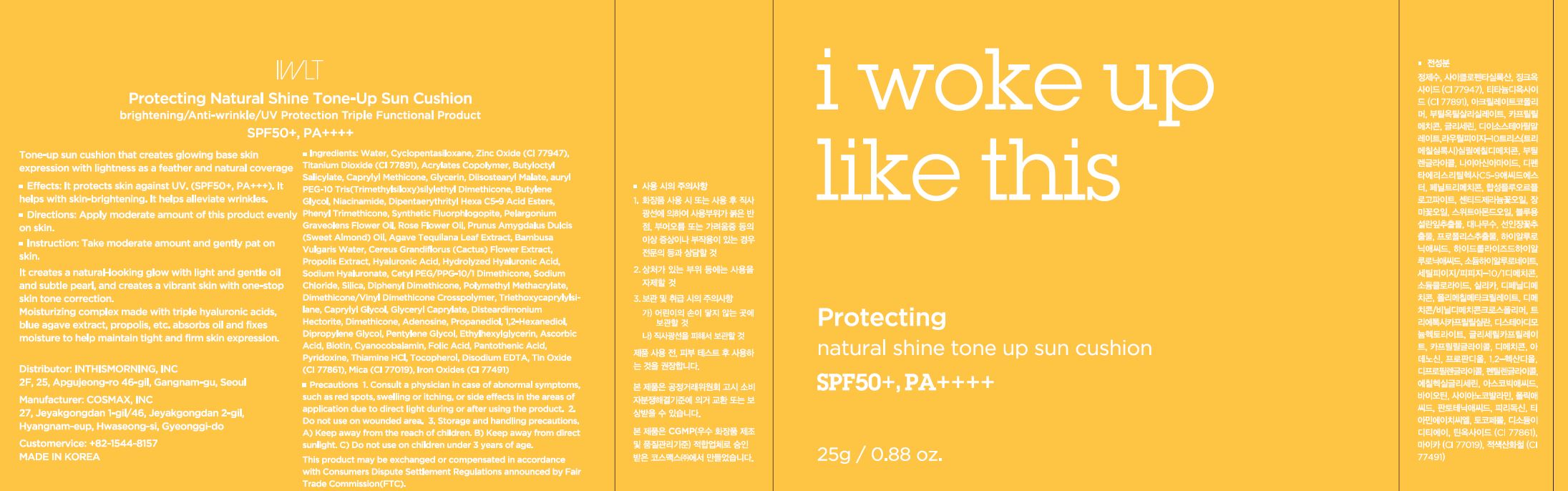 DRUG LABEL: Protecting natural shine tone up sun cushion
NDC: 71217-0059 | Form: POWDER
Manufacturer: inthismorning co ltd
Category: otc | Type: HUMAN OTC DRUG LABEL
Date: 20230130

ACTIVE INGREDIENTS: LINALOOL, (+/-)- 0.0028142856 g/100 g; .BETA.-CITRONELLOL, (R)- 0.03018988 g/100 g; GERANIOL 0.007430248 g/100 g
INACTIVE INGREDIENTS: WATER; GLYCERIN

Drug Facts

ACTIVE INGREDIENT

citronellol, geraniol, linalool

INACTIVE INGREDIENT

Water
Cyclopentasiloxane
Zinc Oxide (CI 77947)
Titanium Dioxide (CI 77891)
Acrylates Copolymer
Butyloctyl Salicylate
Caprylyl Methicone
Glycerin
Diisostearyl Malate
Lauryl PEG-10 Tris(Trimethylsiloxy)silylethyl Dimethicone
Butylene Glycol
Niacinamide
Dipentaerythrityl Hexa C5-9 Acid Esters
Phenyl Trimethicone
Synthetic Fluorphlogopite
Cetyl PEG/PPG-10/1 Dimethicone
Sodium Chloride
Silica
Diphenyl Dimethicone
Mica (CI 77019)
Polymethyl Methacrylate
Dimethicone/Vinyl Dimethicone Crosspolymer
Triethoxycaprylylsilane
Caprylyl Glycol
Glyceryl Caprylate
Disteardimonium Hectorite
Dimethicone
Adenosine
Iron Oxides (CI 77491)l
Disodium EDTA
Pelargonium Graveolens Flower Oil
Tin Oxide (CI 77861)
Rose Flower Oil
Propanediol
Prunus Amygdalus Dulcis (Sweet Almond) Oil
1,2-Hexanediol
Dipropylene Glycol
Pentylene Glycol
Agave Tequilana Leaf Extract
Bambusa Vulgaris Water
Cereus Grandiflorus (Cactus) Flower Extract
Propolis Extract
Ethylhexylglycerin
Hyaluronic Acid
Ascorbic Acid
Biotin
Cyanocobalamin
Folic Acid
Pantothenic Acid
Pyridoxine
Thiamine HCl
Tocopherol
Hydrolyzed Hyaluronic Acid
Sodium Hyaluronate

PURPOSE

brightening, wrinkle care

keep out or reach of the children

INDICATIONS AND USAGE

take moderate amount and gently pat on skin

WARNINGS

This product is for exeternal use only. Do not use for internal use
Storage and handling precautions
If possible, avoid direct sunlight and store in cool and area of low humidity in order to maintain the quality of the product and avoid misuse
Avoid placing the product near fire and store out in reach of children

- consult a physician in case of abnormal symptoms, such as red spots, swelling or itching, or side effects in the areas of application due to direct light during or after using the product

- do not use on wounded area

DOSAGE AND ADMINISTRATION

for external use only